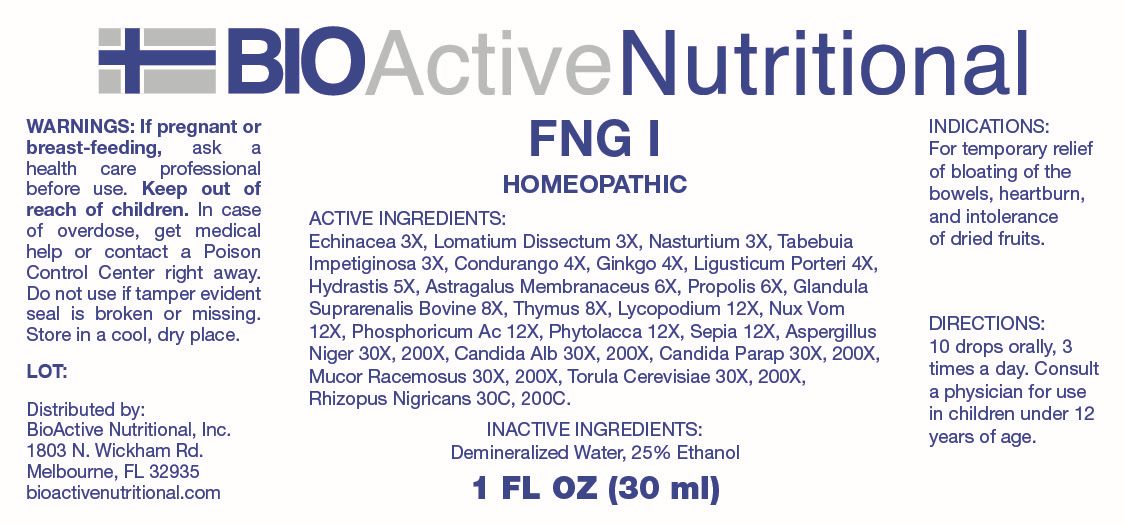 DRUG LABEL: FNG I
NDC: 43857-0802 | Form: LIQUID
Manufacturer: BioActive Nutritional, Inc.
Category: homeopathic | Type: HUMAN OTC DRUG LABEL
Date: 20260120

ACTIVE INGREDIENTS: ECHINACEA ANGUSTIFOLIA WHOLE 3 [hp_X]/1 mL; LOMATIUM DISSECTUM ROOT 3 [hp_X]/1 mL; NASTURTIUM OFFICINALE 3 [hp_X]/1 mL; TABEBUIA IMPETIGINOSA BARK 3 [hp_X]/1 mL; RUEHSSIA CUNDURANGO BARK 4 [hp_X]/1 mL; GINKGO 4 [hp_X]/1 mL; LIGUSTICUM PORTERI ROOT 4 [hp_X]/1 mL; GOLDENSEAL 5 [hp_X]/1 mL; ASTRAGALUS MONGHOLICUS ROOT 6 [hp_X]/1 mL; PROPOLIS WAX 6 [hp_X]/1 mL; BOS TAURUS ADRENAL GLAND 8 [hp_X]/1 mL; BOS TAURUS THYMUS 8 [hp_X]/1 mL; LYCOPODIUM CLAVATUM SPORE 12 [hp_X]/1 mL; STRYCHNOS NUX-VOMICA SEED 12 [hp_X]/1 mL; PHOSPHORIC ACID 12 [hp_X]/1 mL; PHYTOLACCA AMERICANA ROOT 12 [hp_X]/1 mL; SEPIA OFFICINALIS JUICE 12 [hp_X]/1 mL; ALTERNARIA ALTERNATA 30 [hp_X]/1 mL; ASPERGILLUS NIGER VAR. NIGER 30 [hp_X]/1 mL; CANDIDA ALBICANS 30 [hp_X]/1 mL; CANDIDA PARAPSILOSIS 30 [hp_X]/1 mL; SACCHAROMYCES CEREVISIAE 30 [hp_X]/1 mL; MUCOR RACEMOSUS 30 [hp_X]/1 mL; RHIZOPUS STOLONIFER 30 [hp_C]/1 mL
INACTIVE INGREDIENTS: WATER; ALCOHOL

DRUG FACTS:

ACTIVE INGREDIENTS:

Echinacea 3X, Lomatium Dissectum 3X, Nasturtium Aquaticum 3X, Tabebuia Impetiginosa 3X, Condurango 4X, Ginkgo Biloba 4X, Ligusticum Porteri 4X, Hydrastis Canadensis 5X, Astragalus Membranaceus 6X, Propolis 6X, Glandula Suprarenalis Bovine 8X, Thymus 8X, Lycopodium Clavatum 12X, Nux Vomica 12X, Phosphoricum Acidum 12X, Phytolacca Decandra 12X, Sepia 12X, Alternaria Tenuis Nees 30X, 200X, Aspergillus Niger 30X, 200X, Candida Albicans 30X, 200X, Candida Parapsilosis 30X, 200X, Mucor Racemosus 30X, 200X, Torula Cerevisiae 30X, 200X, Rhizopus Nigricans 30C, 200C.

PURPOSE:

For temporary relief of bloating of the bowels, heartburn, and intolerance of dried fruits.

WARNINGS:

If pregnant or breast-feeding, ask a health care professional before use.

Keep out of reach of children. In case of overdose, get medical help or contact a Poison Control Center right away.

Do not use if tamper evident seal is broken or missing.

Store in a cool, dry place.

KEEP OUT OF REACH OF CHILDREN:

In case of overdose, get medical help or contact a Poison Control Center right away.

DIRECTIONS:

10 drops orally, 3 times a day. Consult a physician for use in children under 12 years of age.

INDICATIONS:

For temporary relief of bloating of the bowels, heartburn, and intolerance of dried fruits.

INACTIVE INGREDIENTS:

Demineralized Water, 25% Ethanol

QUESITONS:

Distributed by:
BioActive Nutritional, Inc.
1803 N. Wickham Rd.
Melbourne, FL 32935
bioactivenutritional.com

PACKAGE LABEL DISPLAY:

BIOActiveNutritional

FNG I

HOMEOPATHIC

1 FL OZ (30 ml)